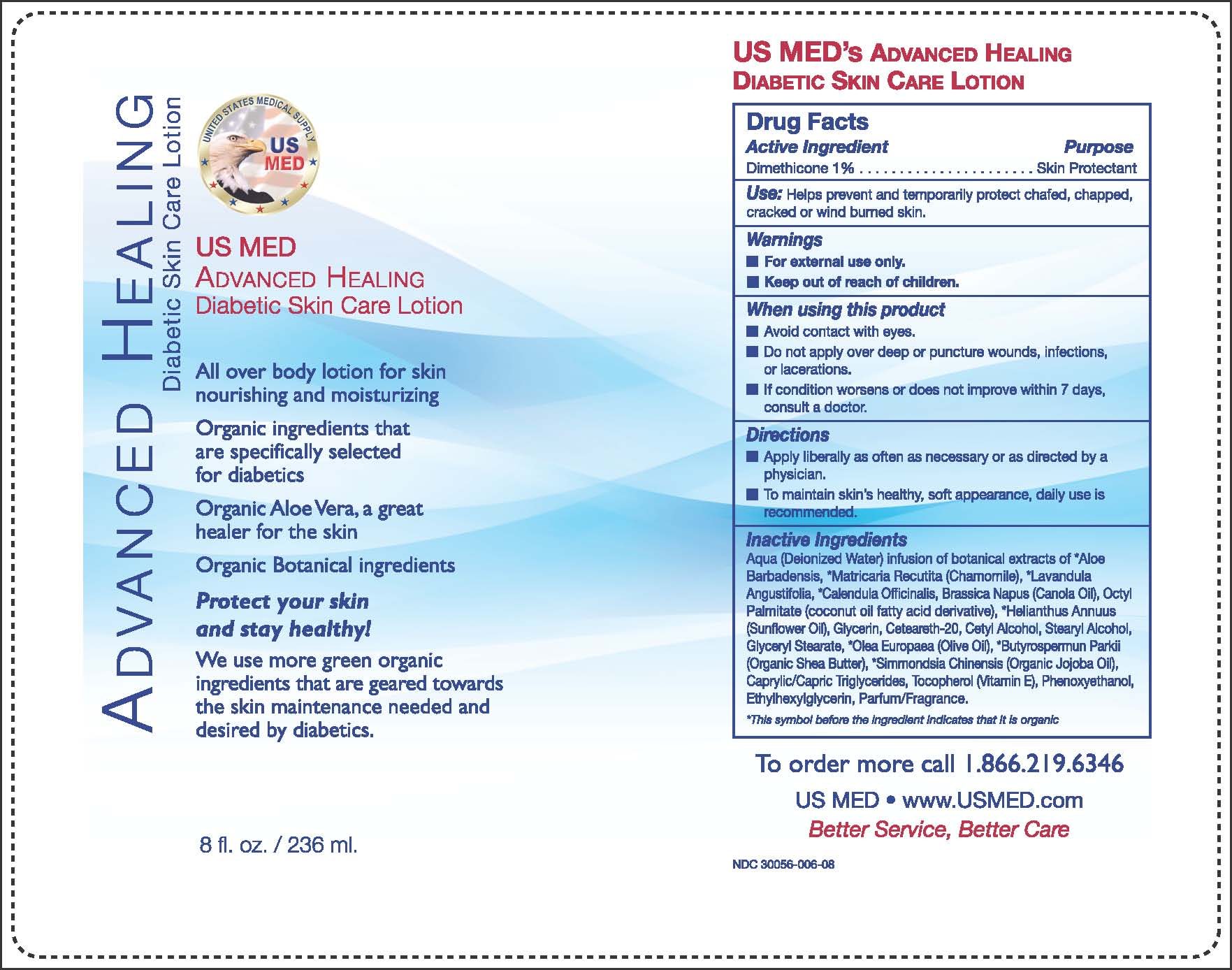 DRUG LABEL: Advanced Healing Diabetic Skin Care
NDC: 30056-006 | Form: LOTION
Manufacturer: Eco-Logics, Inc.
Category: otc | Type: HUMAN OTC DRUG LABEL
Date: 20251018

ACTIVE INGREDIENTS: DIMETHICONE 10 mg/1 g
INACTIVE INGREDIENTS: WATER; ALOE VERA LEAF; CALENDULA OFFICINALIS FLOWER; LAVANDULA ANGUSTIFOLIA FLOWERING TOP; CHAMOMILE; BRASSICA NAPUS OIL; ETHYLHEXYL PALMITATE; SUNFLOWER OIL; GLYCERIN; POLYOXYL 20 CETOSTEARYL ETHER; CETYL ALCOHOL; STEARYL ALCOHOL; GLYCERYL MONOSTEARATE; OLIVE OIL; SHEA BUTTER; JOJOBA OIL; MEDIUM-CHAIN TRIGLYCERIDES; ALPHA-TOCOPHEROL; PHENOXYETHANOL; ETHYLHEXYLGLYCERIN

Advanced Healing Diabetic Skin Care Lotion

Active Ingredients Purpose
Dimethicone 1% Skin Protectant

Purpose

UActive Ingredients Purpose

Dimethicone 1%........... Skin Protectant.

Keep out of reach of children

- If swallowed, get medical help or contact Poison Control Center right away

Directions

- Apply liberally as often as necessary or as directed by a physician.
- To maintain skin's healthy, soft appearance , daily use is recommended.

Warnings

- For external use only.
- Keep out of reach of children.

Uses

Use: Helps prevent and temporaarily protect chafed, chapped, cracked or winburn skin.

When using this product

- Avoid contact with eyes.
- Do not apply over deep or puncture wounds, infections, or lacerations.

Stop use and ask a doctor if

If condition worsens or does not improve within 7 days, or consult a doctor.

If pregnant or breastfeeding , ask a health proferssional before use.

Inactive Ingredients

Aqua(deionozed Water) Infusion of botanical extracts of Aloe Barbadensis, Matricaria Recutita (Chamomile), Lavandula Angustifolia, Calendula Officinalis, Brassica Napus (Canola Oil), Octyl Palmitate (Coconut Oil fatty acid dervative), Helianthus Annuus (Sunflower Oil), Glycerin, Cetyl Alcohol, Stearyl Alcohol, Glyceryl Stearate, Olea Europaea (Olive Oil), Butyrospermun parkii (Organic Shea Butter), Simmondsia chinensis(Organic Jojoba Oil), Caprylic/Capric Triglycerides, Tocopherol (Vitamin E), Parfum/Fragrance.

Directions

Adults and Children 2 years of age and older:

Apply liberally as often as necessary or as directed by a physician.

To maintain skin's healthy, soft appearance, daily use is recommended.

PACKAGE LABEL

Enter section text here